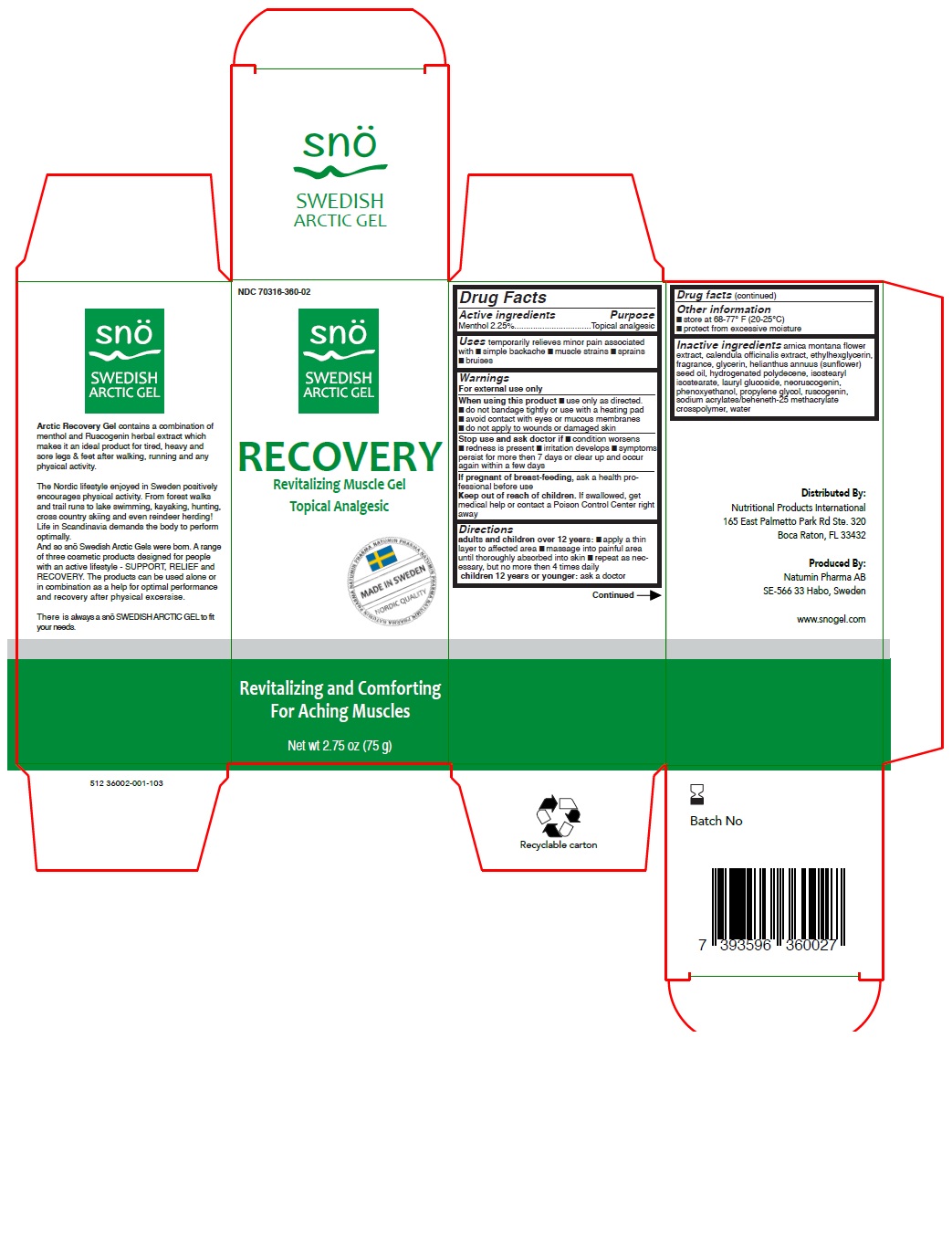 DRUG LABEL: Sno Swedish Arctic Gel Recovery
NDC: 70316-360 | Form: GEL
Manufacturer: Natumin Pharma AB
Category: otc | Type: HUMAN OTC DRUG LABEL
Date: 20151218

ACTIVE INGREDIENTS: MENTHOL, UNSPECIFIED FORM 2.25 g/100 g
INACTIVE INGREDIENTS: SUNFLOWER OIL; HYDROGENATED POLYDECENE (550 MW); LAURYL GLUCOSIDE; PHENOXYETHANOL; PROPYLENE GLYCOL; CALENDULA OFFICINALIS FLOWERING TOP; WATER; GLYCERIN; ISOSTEARYL ISOSTEARATE; RUSCOGENIN; SODIUM ACRYLATE/SODIUM ACRYLOYLDIMETHYLTAURATE COPOLYMER (4000000 MW); ARNICA MONTANA FLOWER; ETHYLHEXYLGLYCERIN

Drug Facts

Active Ingredients

Menthol 2.25%

Purpose

Topical Analgesic

Uses

temporarily relieves minor pain associated with

- simple backache
- muscle strains
- sprains
- bruises

Warning

For external use only

When using this product use only as directed

Do not bandage tightly or use with a heating pad

Avoid contact with eyes or mucous membranes

Do not apply to wounds or damaged skin.

Stop use and ask a doctor if

Condition worsens

Redness is present

Irritation develops

Symptoms persist for more than 7 days or clear up and occur again within a few days

If pregnant or breast feeding,

ask a health professional before use

Keep out of reach of children

If swallowed, get medical help or contact a Poison Control Center right away.

Directions

Adults and children over 12 years:

Apply a thin layer to affected area

Massage into painful area until thoroughly absorbed into skin

Repeat as necessary, but no more than 4 times daily

Children 12 years or younger: ask a doctor

Other Information

Store at 68-77°F (20-25°C).

Protect from excessive moisture.

Inactive Ingredients

Arnica montana flower extract

calendula officinalis extract

ethylhexylglycerin

fragrance

glycerin

helianthus annuus (sunflower) seed oil

hydrongenated polydecene

isostearyl isostearate

lauryl glucoside

neoruscogenin

phenoxyethanol

propylene glycol

ruscogenin

sodium acrylates/beheneth-25 methacrylate crosspolymer

water